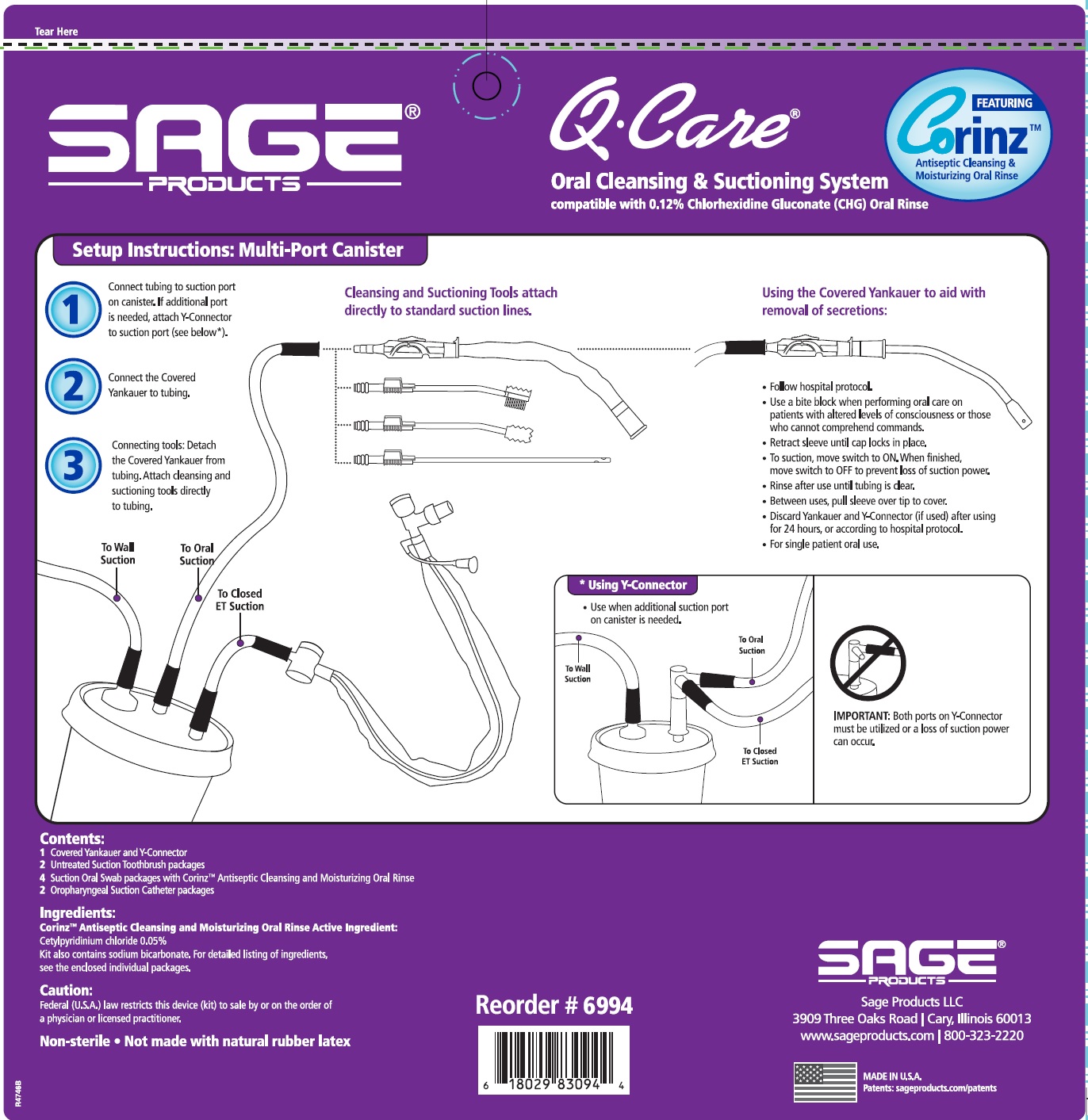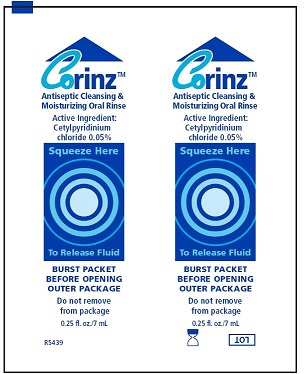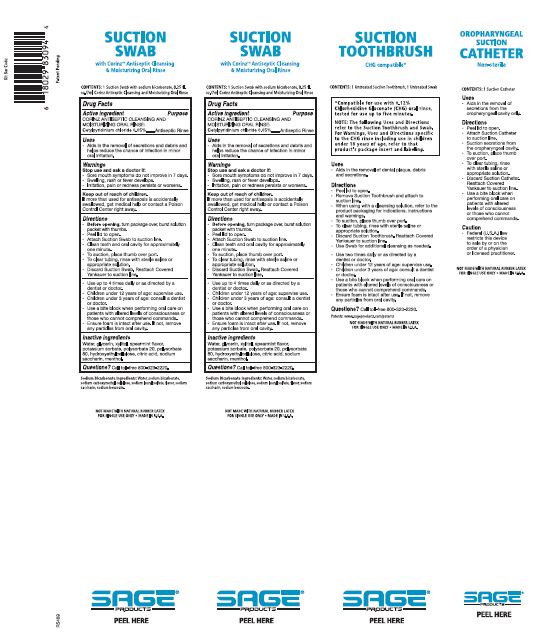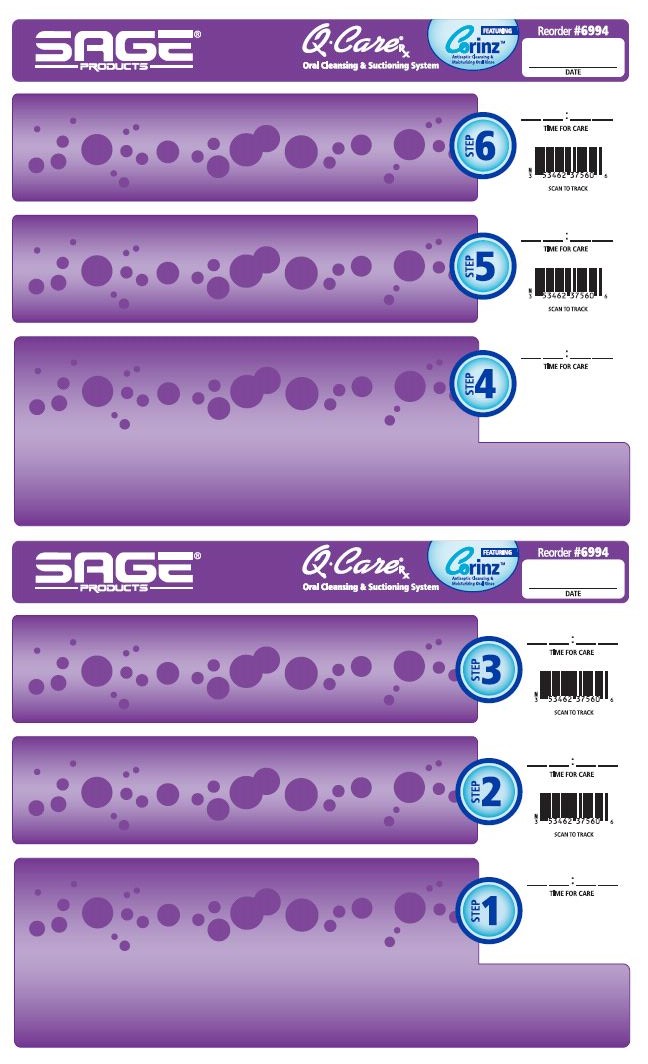 DRUG LABEL: QCare Oral Cleansing and Suctioning System compatible with 0.12% Chlorhexidine Gluconate (CHG) Oral Rinse
NDC: 53462-994 | Form: KIT | Route: ORAL
Manufacturer: Sage Products LLC
Category: otc | Type: HUMAN OTC DRUG LABEL
Date: 20191023

ACTIVE INGREDIENTS: CETYLPYRIDINIUM CHLORIDE 0.5 mg/1 mL
INACTIVE INGREDIENTS: WATER; GLYCERIN; XYLITOL; POTASSIUM SORBATE; POLYSORBATE 20; POLYSORBATE 80; HYDROXYETHYL CELLULOSE (4000 MPA.S AT 1%); CITRIC ACID MONOHYDRATE; SACCHARIN SODIUM; MENTHOL, UNSPECIFIED FORM

QCare Oral Cleansing & Suctioning System compatible with 0.12% Chlorhexidine Gluconate (CHG) Oral Rinse

Drug Facts

Suction Swab with Antiseptic Oral Rinse

Active Ingredient:

Corinz™ Antiseptic Cleansing and Moisturizing Oral Rinse:

Cetylpyridinium chloride 0.05%

Purpose
Antiseptic Rinse

*Compatible for use with 0.12% Chlorhexidine Gluconate (CHG) oral rinse, tested for use up to five minutes.
NOTE: The following Uses and Directions refer to the Suction Toothbrush and Swab. For Warnings, Uses and Directions specific to the CHG rinse including use in children under 18 years of age, refer to that product’s package insert and labeling.

Uses

Suction Swab with Corinz Antiseptic Cleansing and Moisturizing Oral Rinse

- Aids in the removal of secretions and debris and helps reduce the chance of infection in minor oral irritation.

Suction Toothbrush CHG compatible*

- Aids in the removal of dental plaque, debris and secretions.

Oropharyngeal Suction Catheter Non-sterile

- Aids in the removal of secretions from the oropharyngeal cavity only.

WARNINGS

Stop use and ask a doctor if:
- Sore mouth symptoms do not improve in 7 days.
- Swelling, rash or fever develops.
- Irritation, pain or redness persists or worsens.

Keep out of reach of children.
If more than used for antisepsis is accidentally swallowed, get medical help or contact a Poison Control Center right away.

Directions

Suction Swab with Antiseptic Oral Rinse
Before opening, turn package over, burst solution packet with thumbs.

- Peel lid to open.
- Remove Mouth Moisturizer and Applicator Swab.
- Attach Suction Swab to suction line.
- Clean teeth and oral cavity for approximately one minute.
- To suction, place thumb over port.
- To clear tubing, rinse with sterile saline or appropriate solution.
- Discard Suction Swab. Reattach Covered Yankauer to suction line.
- Place Mouth Moisturizer on Applicator Swab.
- Apply as needed to lips and inside mouth.
- Use up to 4 times daily or as directed by a dentist or doctor.
- Children under 12 years of age: supervise use.
- Children under 3 years of age: consult a dentist or doctor.
- Use a bite block when performing oral care on patients with altered levels of consciousness or those who cannot comprehend commands.
- Ensure foam is intact after use. If not, remove any particles from oral cavity.

Suction Toothbrush CHG compatible*

- Peel lid to open.
- Remove Suction Toothbrush and attach to suction line.
- When using with a cleansing solution, refer to the product packaging for indications, instructions and warnings.
- To suctions, place thumb over port.
- To clear tubing, rinse with sterile saline or appropriate solution.
- Discard Suction Toothbrush. Reattach Covered Yankauer to suction line.
- Use Swab for additional cleansing as needed.
- Use two times daily or as directed by a dentist or doctor.
- Children under 12 years of age: supervise use.
- Children under 3 years of age: consult a dentist or doctor.
- Use a bite block when performing oral care on patients with altered levels of consciousness or those who cannot comprehend commands.
- Ensure foam is intact after use. If not, remove any particles from oral cavity.

Oropharyngeal Suction Catheter Non-sterile

- Peel lid to open.
- Attach Suction Catheter to suction line.
- Suction secretions from the oropharyngeal cavity.
- To suction, place thumb over port.
- To clear tubing, rinse with sterile saline or appropriate solution.
- Discard Suction Catheter. Reattach Covered Yankauer to suction line.
- Use a bite block when performing oral care on patients with altered levels of consciousness or those who cannot comprehend commands.
- Oropharyngeal Suction Catheter Non-sterile

Caution

- Federal (U.S.A.) law restricts this device to sale by or on the order of a physician or licensed practitioner.

Inactive Ingredients

Suction Swab with Corinz Antiseptic Cleansing and Moisturizing Oral Rinse

Water, glycerin, xylitol, spearmint flavor, potassium sorbate, polysorbate 20, polysorbate 80, hydroxyethylcellulose, citric acid, sodium saccharin, menthol.

Questions?

Call toll-free 800–323–2220

NOT MADE WITH NATURAL RUBBER LATEX • FOR SINGLE USE ONLY • MADE IN U.S.A.

Manufactured for:
Sage Products LLC
Cary, IL 60013

1-800-323-2220